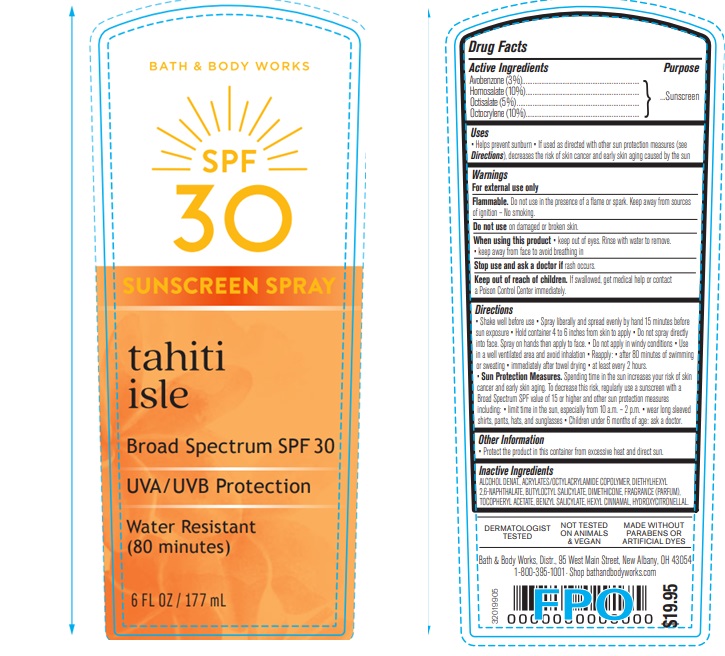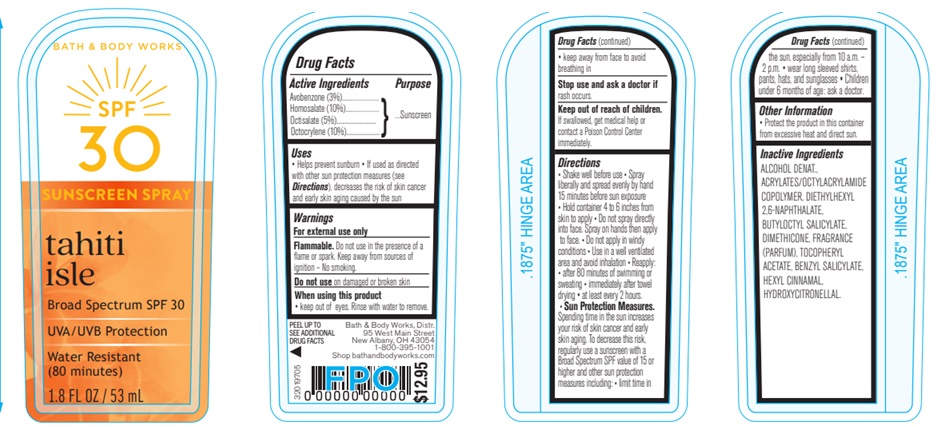 DRUG LABEL: Bath and Body Works SPF
NDC: 62670-6858 | Form: SPRAY
Manufacturer: Bath & Body Works, Inc.
Category: otc | Type: HUMAN OTC DRUG LABEL
Date: 20260302

ACTIVE INGREDIENTS: OCTOCRYLENE 10 mg/100 mg; AVOBENZONE 3 mg/100 mg; HOMOSALATE 10 mg/100 mg; OCTISALATE 5 mg/100 mg
INACTIVE INGREDIENTS: WATER

SPF Spray Tahiti Isle

Active Ingredients

Avobenzone 3%, Homosalate 10%, Octisalate 5%, Octocrylene 10%

Purpose

Sunscreen

Warnings

For external use only

Flammable.

Do not use in the presence of a flame or spark. Keep away from sources of ignition -- No smoking. Do not use on damaged or broken skin

When using this product

keep out of eyes. Rinse with water to remove.

- keep away from face to avoid breathing in

Stop use and ask a doctor

if rash occurs

Keep out of reach of children

If product is swallowed, get medical help or contact a Poison Control Center immediately.

Uses

• helps prevent sunburn • if used as directed with other sun protection measures (see Directions), decreases the risk of skin cancer and early skin aging caused by the sun

Directions

•Shake well before use. •Spray liberally and spread evenly by hand 15 minutes before sun exposure •Hold container 4-6 inches from skin to apply •Do not spray directly into face. Spray on hands then apply to face. •Do not apply in windy conditions •Use in a well ventilated area and avoid inhalation • Reapply: • after 80 minutes of swimming or sweating • immediately after towel drying • at least every 2 hours • Sun Protection Measures. Spending time in the sun increases your risk of skin cancer and early skin aging. To decrease this risk, regularly use a sunscreen with a broad spectrum SPF of 15 or higher and other sun protection measures including: • limit time in the sun, especially from 10 a.m. - 2 p.m. • wear long-sleeved shirts, pants, hats, and sunglasses • children under 6 months: Ask a doctor

Inactive ingredients

Alcohol Denat., Acrylates/Octylacrylamide Copolymer, Diethylhexyl 2,6-Naphthalate, Butyloctyl Salicylate, Dimethicone, Fragrance (Parfum), Tocopheryl Acetate, Benzyl Salicylate, Hexyl Cinnamal, Hydroxycitronellal.

Other information

• protect this product from excessive heat and direct sun

Bath & Body Works, Distr.

95 West Main Street New Albany, OH 43054

1-800-395-1001

shop bathandbodyworks.com